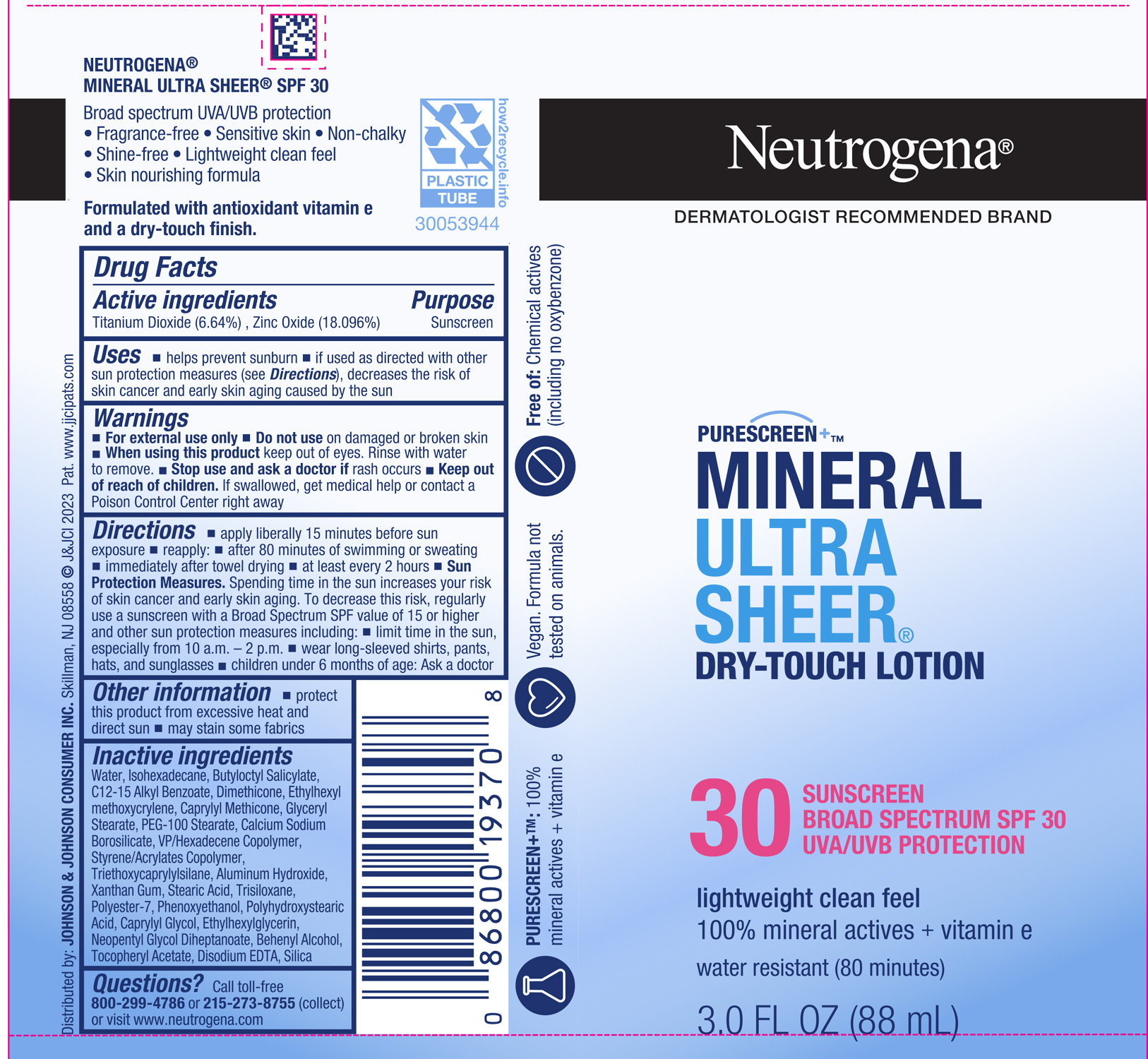 DRUG LABEL: Neutrogena Mineral Ultra Sheer Dry Touch SPF 30
NDC: 69968-0776 | Form: LOTION
Manufacturer: Kenvue Brands LLC
Category: otc | Type: HUMAN OTC DRUG LABEL
Date: 20250213

ACTIVE INGREDIENTS: ZINC OXIDE 180 mg/1 mL; TITANIUM DIOXIDE 66 mg/1 mL
INACTIVE INGREDIENTS: ISOHEXADECANE; ALKYL (C12-15) BENZOATE; CAPRYLYL TRISILOXANE; GLYCERYL MONOSTEARATE; CAPRYLYL GLYCOL; NEOPENTYL GLYCOL DIHEPTANOATE; ETHYLHEXYL METHOXYCRYLENE; VINYLPYRROLIDONE/HEXADECENE COPOLYMER; BUTYL METHACRYLATE/METHYL METHACRYLATE/METHACRYLIC ACID/STYRENE CROSSPOLYMER; ALUMINUM HYDROXIDE; XANTHAN GUM; PHENOXYETHANOL; ETHYLHEXYLGLYCERIN; DOCOSANOL; ALPHA-TOCOPHEROL ACETATE; EDETATE DISODIUM ANHYDROUS; SILICON DIOXIDE; WATER; BUTYLOCTYL SALICYLATE; DIMETHICONE; TRISILOXANE; CALCIUM SODIUM BOROSILICATE; PEG-100 STEARATE; TRIETHOXYCAPRYLYLSILANE; STEARIC ACID; POLYESTER-7

Neutrogena Mineral Ultra Sheer Dry Touch Lotion SPF 30

Drug Facts

ACTIVE INGREDIENT

Active ingredients | Purpose
Titanium Dioxide (6.6%) Zinc Oxide (18.0%) | Sunscreen

Uses

- helps prevent sunburn
- if used as directed with other sun protection measures (see Directions), decreases the risk of skin cancer and early skin aging caused by the sun

Warnings

For external use only

Do not use on damaged or broken skin

When using this product keep out of eyes. Rinse with water to remove.

Stop use and ask a doctor if rash occurs

Keep out of reach of children. If swallowed, get medical help or contact a Poison Control Center right away

Directions

- apply liberally 15 minutes before sun exposure
- reapply:
- after 80 minutes of swimming or sweating
- immediately after towel drying
- at least every 2 hours
- Sun Protection Measures. Spending time in the sun increases your risk of skin cancer and early skin aging. To decrease this risk, regularly use a sunscreen with a Broad Spectrum SPF value of 15 or higher and other sun protection measures including:
- limit time in the sun, especially from 10 a.m. – 2 p.m.
- wear long-sleeved shirts, pants, hats, and sunglasses
- children under 6 months of age: Ask a doctor

Other information

- protect this product from excessive heat and direct sun
- may stain some fabrics

Inactive ingredients

Water, Isohexadecane, Butyloctyl Salicylate, C12-15 Alkyl Benzoate, Dimethicone, Ethylhexyl methoxycrylene, Caprylyl Methicone, Glyceryl Stearate, PEG-100 Stearate, Calcium Sodium Borosilicate, VP/Hexadecene Copolymer, Styrene/Acrylates Copolymer, Triethoxycaprylylsilane, Aluminum Hydroxide, Xanthan Gum, Stearic Acid, Trisiloxane, Polyester-7, Phenoxyethanol, Polyhydroxystearic Acid, Caprylyl Glycol, Ethylhexylglycerin, Neopentyl Glycol Diheptanoate, Behenyl Alcohol, Tocopheryl Acetate, Disodium EDTA, Silica

Questions?

Call toll-free 800-299-4786 or 215-273-8755 (collect) or visit www.neutrogena.com

Distributed by: JOHNSON & JOHNSON CONSUMER INC. Skillman, NJ 08558

PRINCIPAL DISPLAY PANEL - 88 mL Tube Label

Neutrogena®

DERMATOLOGIST RECOMMENED BRAND

PURESCREEN+TM

MINERAL

ULTRA

SHEER®

DRY-TOUCH LOTION

30

SUNSCREEN

BROAD SPECTRUM SPF 30

UVA/UVB PROTECTION

lightweight clean feel

100% mineral actives + vitamin e

water resistant (80 minutes)

3.0 FL OZ (88 mL)